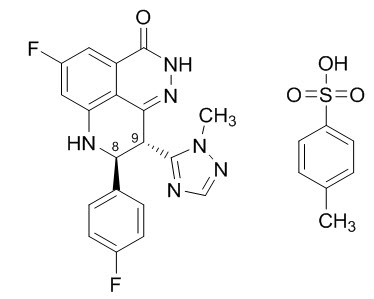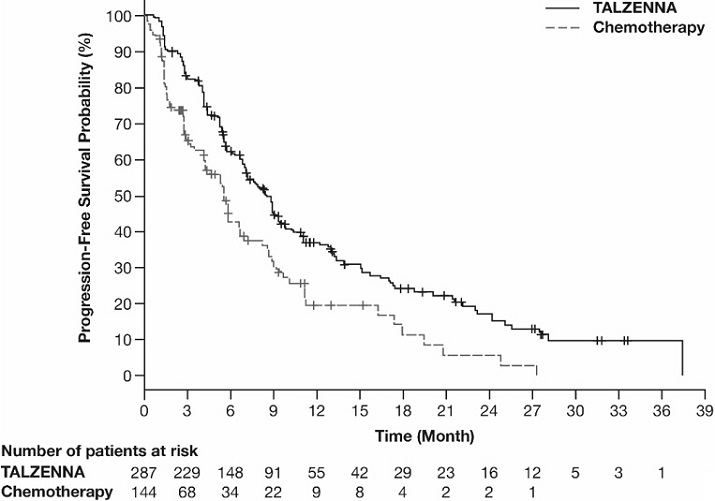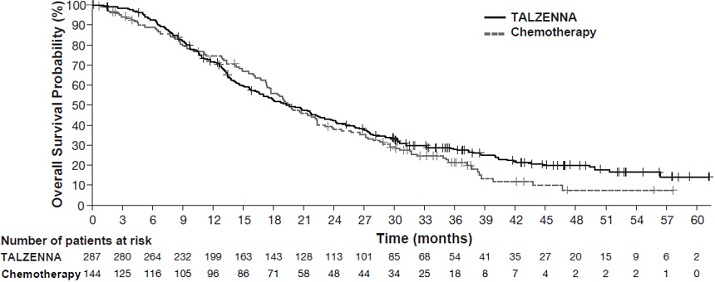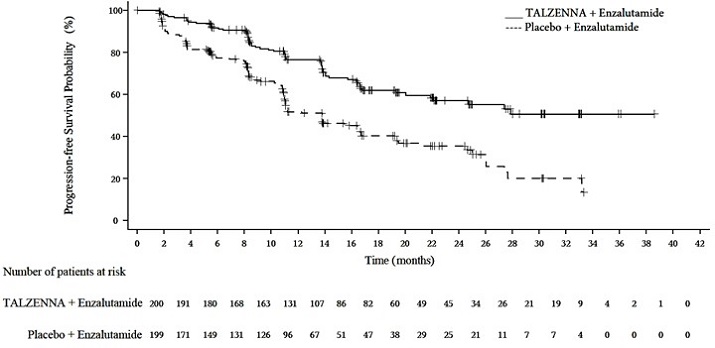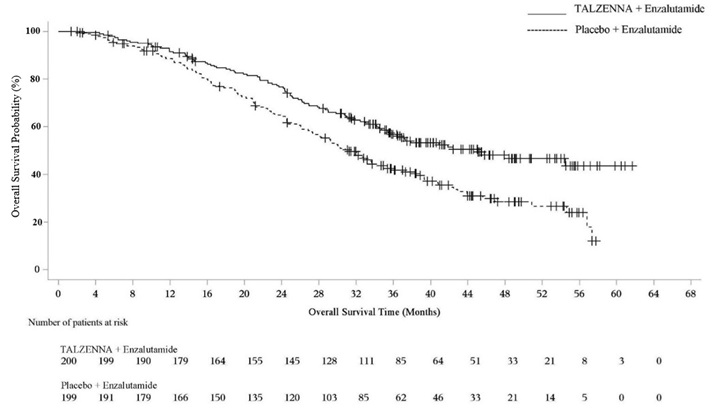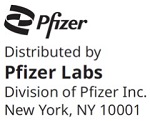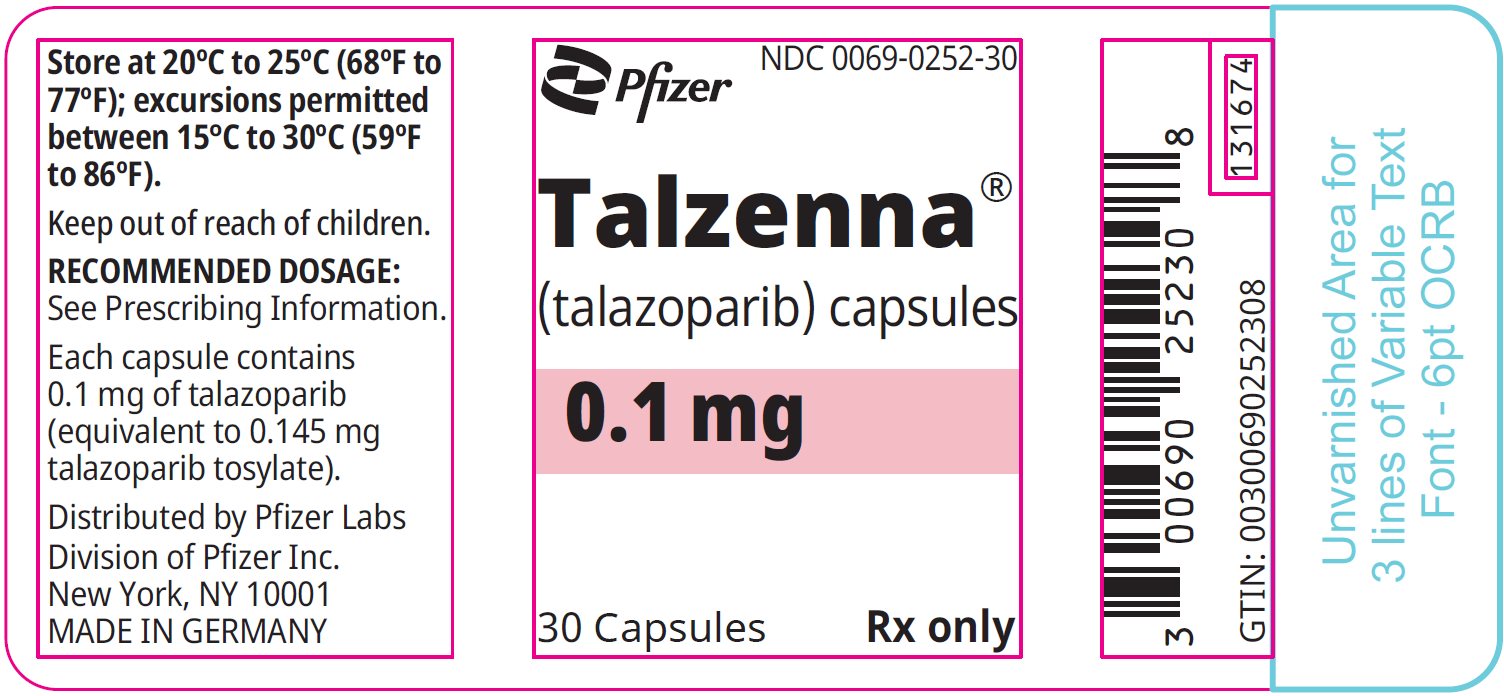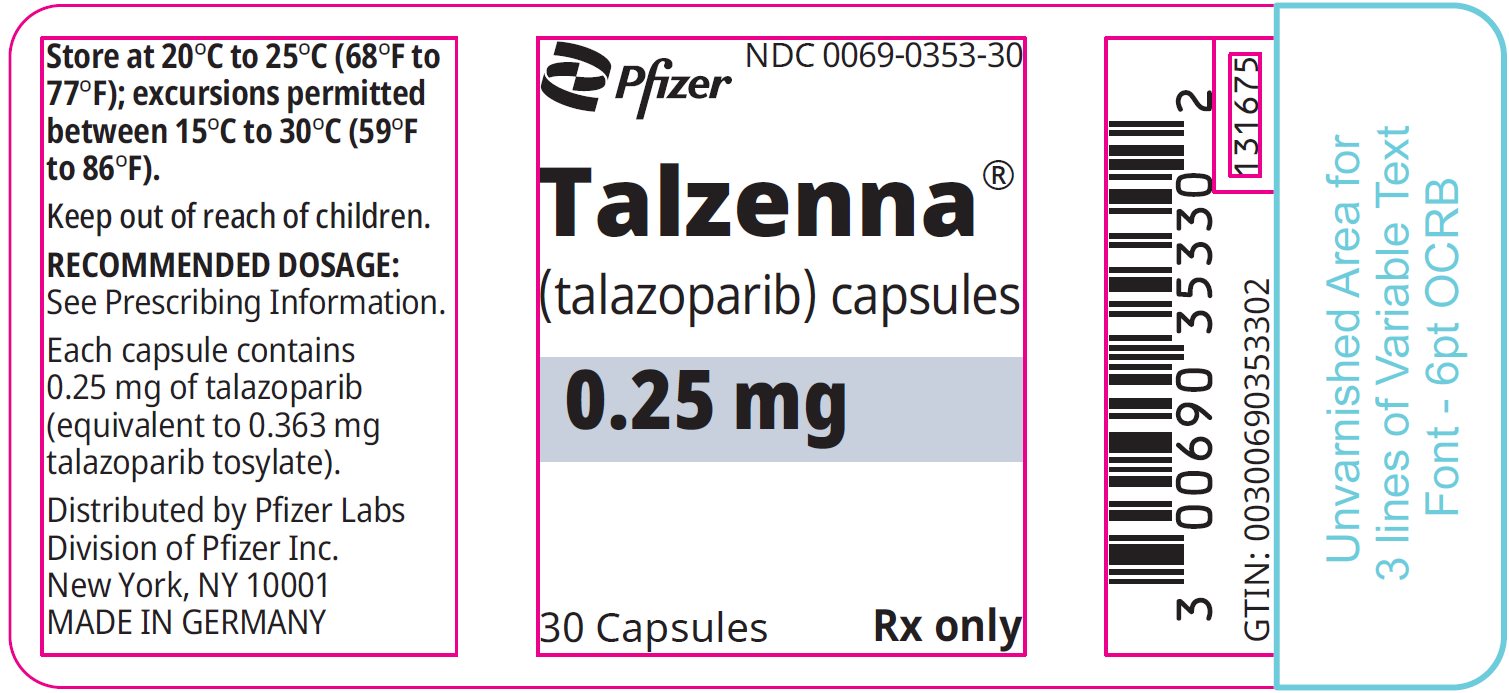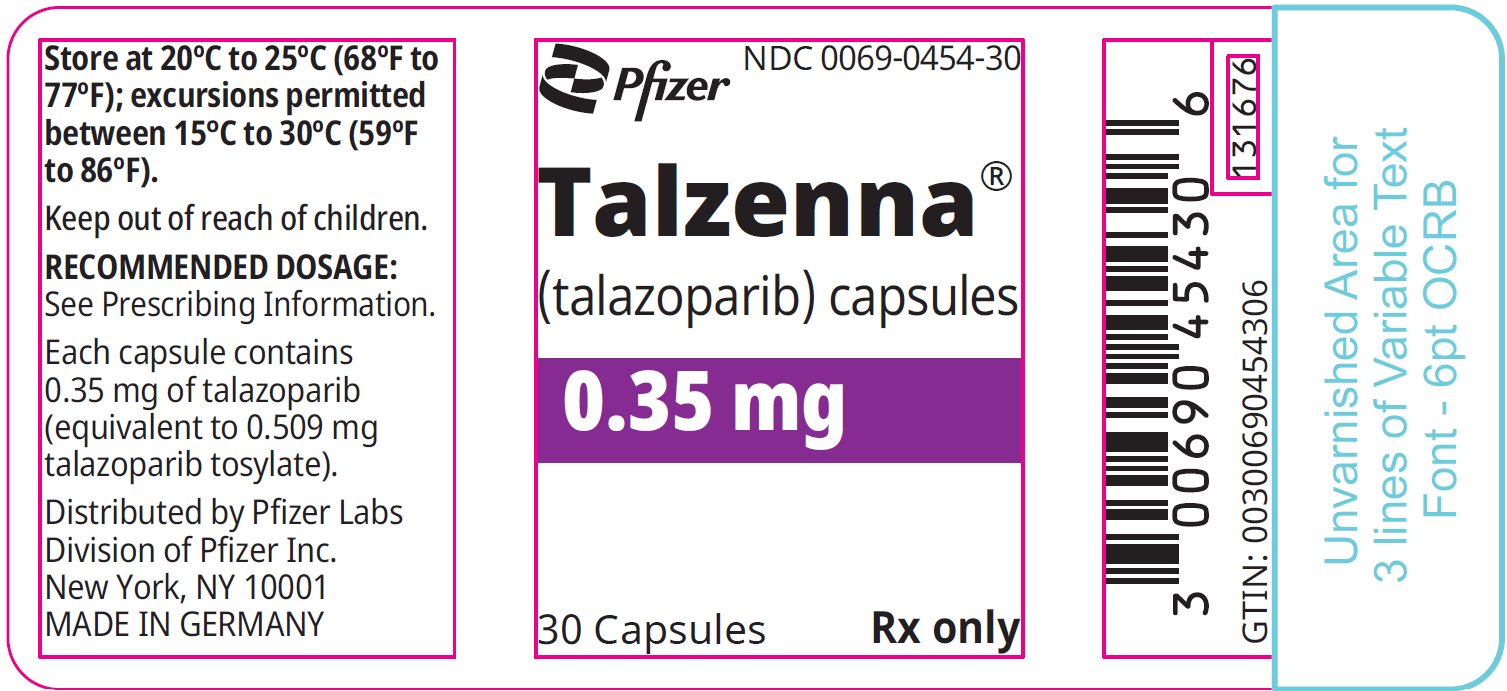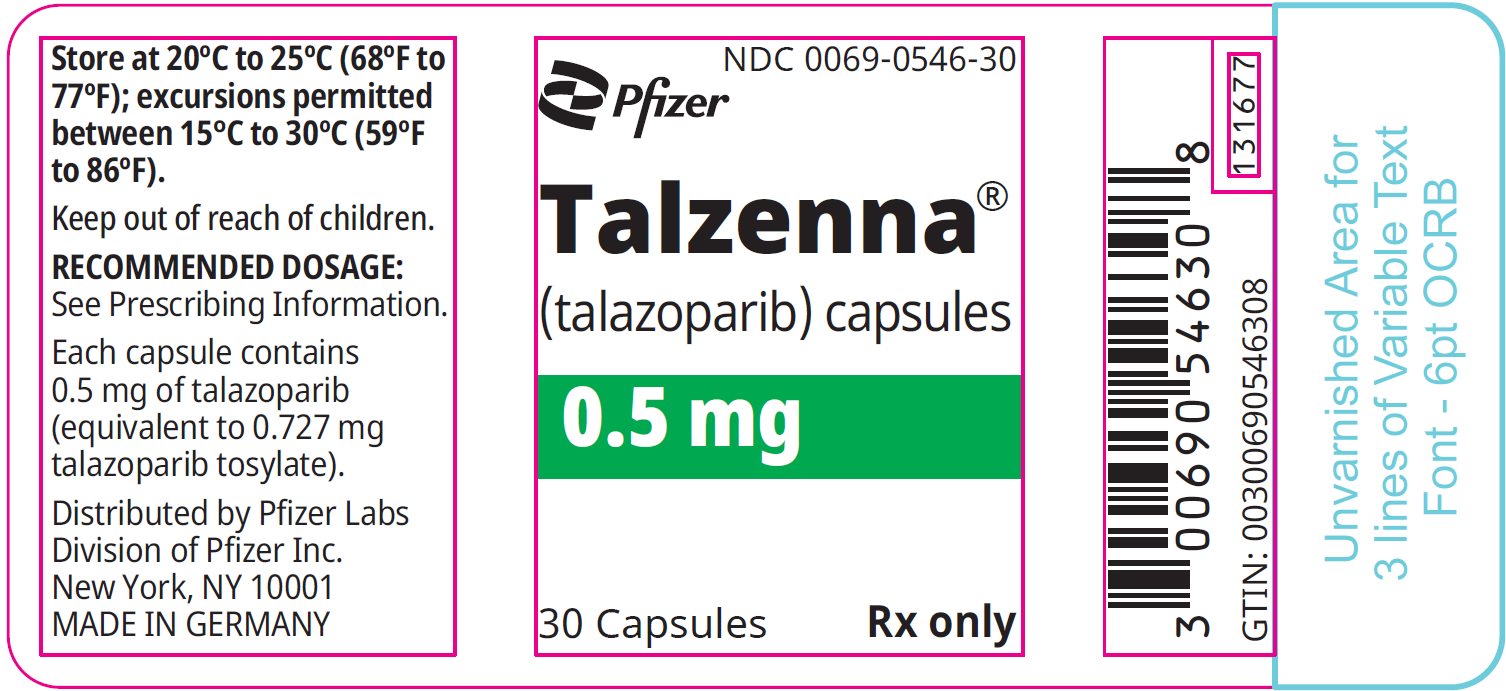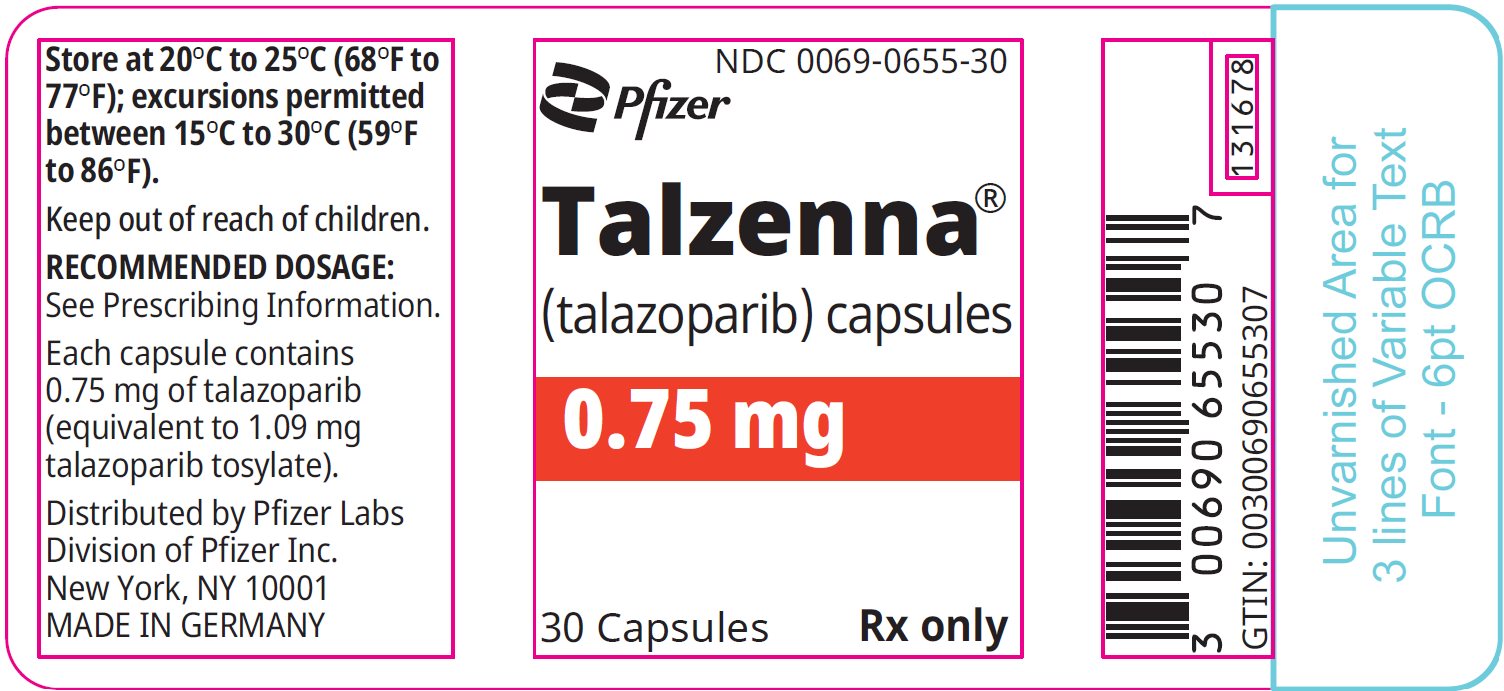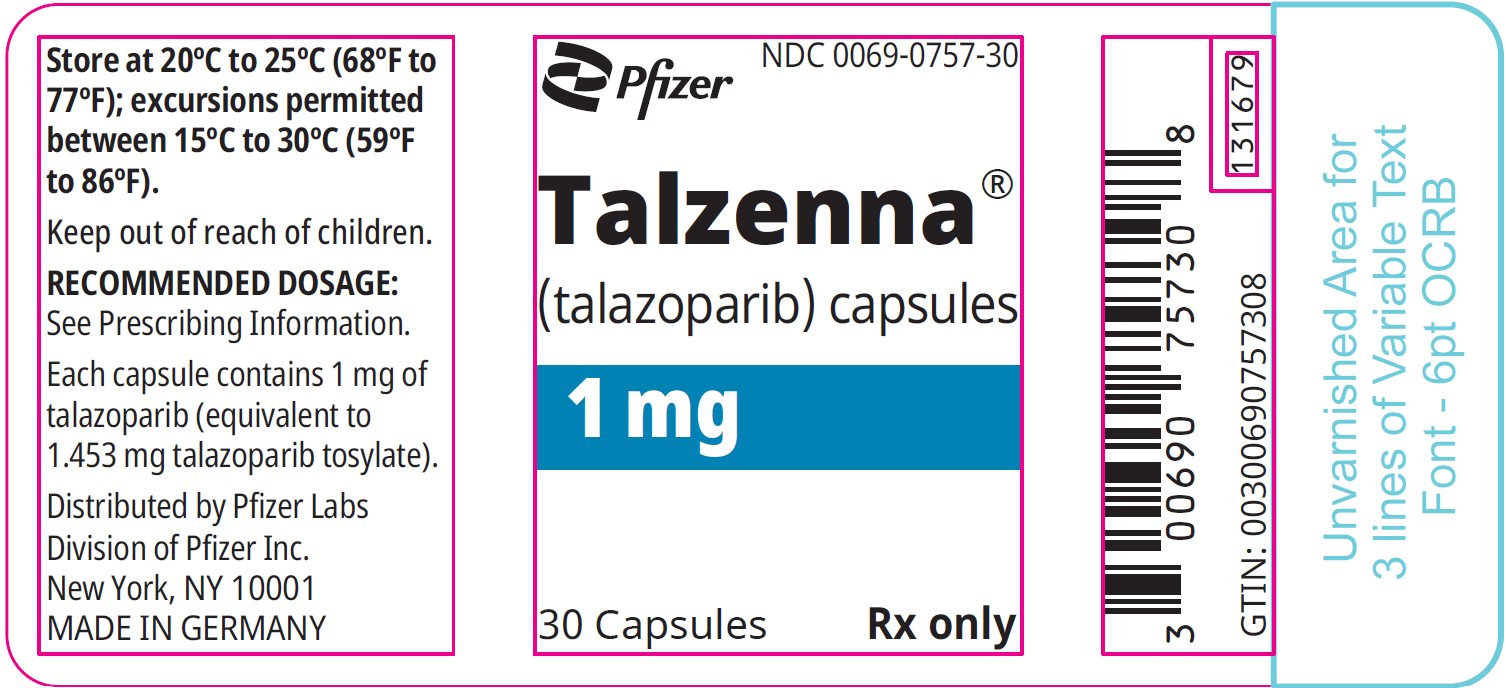 DRUG LABEL: Talzenna
NDC: 0069-0252 | Form: CAPSULE, LIQUID FILLED
Manufacturer: Pfizer Laboratories Div Pfizer Inc
Category: prescription | Type: HUMAN PRESCRIPTION DRUG LABEL
Date: 20250619

ACTIVE INGREDIENTS: TALAZOPARIB TOSYLATE 0.1 mg/1 1
INACTIVE INGREDIENTS: POLYETHYLENE GLYCOL 400; GLYCERIN; .ALPHA.-TOCOPHEROL; GELATIN TYPE A PORCINE (195 BLOOM); SORBITOL; FERRIC OXIDE RED; TITANIUM DIOXIDE; WATER

HIGHLIGHTS OF PRESCRIBING INFORMATION

These highlights do not include all the information needed to use TALZENNA safely and effectively. See full prescribing information for TALZENNA.
TALZENNA® (talazoparib) capsules, for oral use
Initial U.S. Approval: 2018

1 INDICATIONS AND USAGE

TALZENNA is a poly (ADP-ribose) polymerase (PARP) inhibitor indicated for:

Breast Cancer

- As a single agent, for the treatment of adult patients with deleterious or suspected deleterious germline BRCA-mutated (gBRCAm) HER2-negative locally advanced or metastatic breast cancer. Select patients for therapy based on an FDA-approved companion diagnostic for TALZENNA. (1.1)

HRR Gene-mutated Metastatic Castration-Resistant Prostate Cancer (mCRPC)

- In combination with enzalutamide for the treatment of adult patients with HRR gene-mutated metastatic castration-resistant prostate cancer (mCRPC). (1.2)

2 DOSAGE AND ADMINISTRATION

- Take TALZENNA with or without food. (2.4)

Breast Cancer

- The recommended dosage of TALZENNA is 1 mg taken orally once daily until disease progression or unacceptable toxicity. (2.2)
- For adverse reactions, consider dosing interruption or dose reduction. (2.5)

HRR Gene-mutated Metastatic Castration-Resistant Prostate Cancer (mCRPC)

- The recommended dosage of TALZENNA is 0.5 mg taken orally once daily with enzalutamide until disease progression or unacceptable toxicity. (2.3)
- Patients should also receive a gonadotropic-releasing hormone (GnRH) analog concurrently or should have had bilateral orchiectomy. (2.3)

3 DOSAGE FORMS AND STRENGTHS

Capsules: 0.1 mg, 0.25 mg, 0.35 mg, 0.5 mg, 0.75 mg, and 1 mg (3)

4 CONTRAINDICATIONS

None. (4)

5 WARNINGS AND PRECAUTIONS

- Myelodysplastic Syndrome/Acute Myeloid Leukemia (MDS/AML): MDS/AML occurred in patients exposed to TALZENNA, and some cases were fatal. Monitor patients for hematological toxicity and discontinue if MDS/AML is confirmed. (5.1)
- Myelosuppression: TALZENNA may affect hematopoiesis and can cause anemia, neutropenia, and/or thrombocytopenia. (5.2)
- Embryo-Fetal Toxicity: TALZENNA can cause fetal harm. Advise of the potential risk to the fetus and to use effective contraception. (5.3, 8.1, 8.3)

6 ADVERSE REACTIONS

Most common adverse reactions (≥20%) as a single agent, including laboratory abnormalities, are:

- Hemoglobin decreased, neutrophils decreased, lymphocytes decreased, platelets decreased, fatigue, glucose increased, aspartate aminotransferase increased, alkaline phosphatase increased, alanine aminotransferase increased, calcium decreased, nausea, headache, vomiting, alopecia, diarrhea, and decreased appetite. (6.1)

Most common adverse reactions (≥10%) in combination with enzalutamide, including laboratory abnormalities, are:

- Hemoglobin decreased, neutrophils decreased, lymphocytes decreased, fatigue, platelets decreased, calcium decreased, nausea, decreased appetite, sodium decreased, phosphate decreased, fractures, magnesium decreased, dizziness, bilirubin increased, potassium decreased, and dysgeusia. (6.1)

To report SUSPECTED ADVERSE REACTIONS, contact Pfizer Inc. at 1-800-438-1985 or FDA at 1-800-FDA-1088 or www.fda.gov/medwatch.

7 DRUG INTERACTIONS

- P-gp Inhibitors: Reduce the dose when coadministered with certain P-gp inhibitors. Monitor for increased adverse reactions. (2.7, 7.1)
- BCRP Inhibitors: Monitor for potential increased adverse reactions. (7.1)

8 USE IN SPECIFIC POPULATIONS

- Lactation: Advise women not to breastfeed. (8.2)
- Renal Impairment: Reduce the dose and monitor for increased adverse reactions for patients with moderate or severe renal impairment. (2.6, 8.7)

FULL PRESCRIBING INFORMATION

1 INDICATIONS AND USAGE

1.1 BRCA-mutated (gBRCAm) HER2-negative Locally Advanced or Metastatic Breast Cancer

TALZENNA is indicated as a single agent for the treatment of adult patients with deleterious or suspected deleterious germline breast cancer susceptibility gene (BRCA)-mutated (gBRCAm) human epidermal growth factor receptor 2 (HER2)-negative locally advanced or metastatic breast cancer. Select patients for therapy based on an FDA-approved companion diagnostic for TALZENNA [see Dosage and Administration (2.1)].

1.2 HRR Gene-mutated Metastatic Castration-Resistant Prostate Cancer (mCRPC)

TALZENNA is indicated in combination with enzalutamide for the treatment of adult patients with homologous recombination repair (HRR) gene-mutated metastatic castration-resistant prostate cancer (mCRPC) [see Dosage and Administration (2.3)].

2 DOSAGE AND ADMINISTRATION

2.1 Patient Selection

Information on the FDA-approved tests for the detection of genetic mutations is available at http://www.fda.gov/companiondiagnostics.

gBRCAm HER2-negative Locally Advanced or Metastatic Breast Cancer

Select patients for the treatment of advanced breast cancer with TALZENNA based on the presence of germline BRCA mutations [see Indications and Usage (1.1), Clinical Studies (14.1)].

HRR Gene-mutated Metastatic Castration-Resistant Prostate Cancer

Select patients for the treatment of HRR gene-mutated mCRPC with TALZENNA based on the presence of alterations in genes directly or indirectly involved in HRR (ATM, ATR, BRCA1, BRCA2, CDK12, CHEK2, FANCA, MLH1, MRE11A, NBN, PALB2, or RAD51C) [see Indications and Usage (1.2), Clinical Studies (14.2)].

An FDA-approved test for the detection of HRR gene mutations for use with TALZENNA is not currently available.

2.2 Recommended Dosage for gBRCAm HER2-negative Locally Advanced or Metastatic Breast Cancer

The recommended dosage of TALZENNA is 1 mg taken orally once daily, until disease progression or unacceptable toxicity.

2.3 Recommended Dosage for HRR Gene-mutated mCRPC

The recommended dosage of TALZENNA is 0.5 mg taken orally once daily with enzalutamide until disease progression or unacceptable toxicity.

Refer to the enzalutamide prescribing information for recommended enzalutamide dosing information.

Patients receiving TALZENNA and enzalutamide should also receive a gonadotropin-releasing hormone (GnRH) analog concurrently or should have had bilateral orchiectomy.

2.4 Administration

Take TALZENNA with or without food.

Swallow TALZENNA capsules whole. Do not open or dissolve.

If a patient vomits or misses a dose of TALZENNA, instruct them to take the next prescribed dose at the usual time.

2.5 Dosage Modifications for Adverse Reactions

To manage adverse reactions, consider interruption of treatment with or without dose reduction based on severity and clinical presentation. Recommended dose reductions are indicated in Table 1 and Table 2. Treatment with TALZENNA should be discontinued if more than 3 dose reductions are required.

gBRCAm HER2-negative Locally Advanced or Metastatic Breast Cancer

Table 1. Dose Reduction Levels for Adverse Reactions—Breast Cancer
Dose Reductions | Dose Level
Recommended starting dose | 1 mg once daily
First dose reduction | 0.75 mg once daily
Second dose reduction | 0.5 mg once daily
Third dose reduction | 0.25 mg once daily

HRR Gene-mutated mCRPC

Table 2. Dose Reduction Levels for Adverse Reactions—mCRPC
Dose Reductions | Dose Level
Recommended starting dose | 0.5 mg once daily
First dose reduction | 0.35 mg once daily
Second dose reduction | 0.25 mg once daily
Third dose reduction | 0.1 mg once daily

Refer to the enzalutamide prescribing information for dose modifications for adverse reactions associated with enzalutamide.

gBRCAm HER2-negative Locally Advanced or Metastatic Breast Cancer and HRR Gene-mutated mCRPC

Monitor complete blood counts monthly and as clinically indicated [see Warnings and Precautions (5.2)].

Table 3. Dose Modification and Management for Adverse Reactions
Adverse Reactions | Withhold TALZENNA Until Levels Resolve to | Resume TALZENNA
Hemoglobin <8 g/dL | ≥9 g/dL | Resume TALZENNA at a reduced dose
Platelet count <50,000/μL | ≥75,000/μL | Resume TALZENNA at a reduced dose
Neutrophil count <1,000/μL | ≥1500/µL | Resume TALZENNA at a reduced dose
Non-hematologic Grade 3 or Grade 4 | ≤Grade 1 | Consider resuming TALZENNA at a reduced dose or discontinue

2.6 Recommended Dosage in Patients with Renal Impairment

gBRCAm HER2-negative Locally Advanced or Metastatic Breast Cancer

The recommended dosage of TALZENNA for patients with moderate renal impairment (CLcr 30 - 59 mL/min) is 0.75 mg taken orally once daily [see Use in Specific Populations (8.7)].

The recommended dosage of TALZENNA for patients with severe renal impairment (CLcr 15 - 29 mL/min) is 0.5 mg taken orally once daily [see Use in Specific Populations (8.7)].

HRR Gene-mutated mCRPC

The recommended dosage of TALZENNA for patients with moderate renal impairment (CLcr 30 - 59 mL/min) is 0.35 mg taken orally once daily with enzalutamide [see Use in Specific Populations (8.7)].

The recommended dosage of TALZENNA for patients with severe renal impairment (CLcr 15 - 29 mL/min) is 0.25 mg taken orally once daily with enzalutamide [see Use in Specific Populations (8.7)].

2.7 Dosage Modifications for P-glycoprotein Inhibitors

gBRCAm HER2-negative Locally Advanced or Metastatic Breast Cancer

Avoid coadministration of TALZENNA with the following P-glycoprotein (P-gp) inhibitors: itraconazole, amiodarone, carvedilol, clarithromycin, itraconazole, and verapamil. If coadministration of TALZENNA with these P-gp inhibitors cannot be avoided, reduce the dose of TALZENNA to 0.75 mg taken orally once daily. When the P-gp inhibitor is discontinued, increase the dose of TALZENNA (after 3 – 5 half-lives of the P-gp inhibitor) to the dose of TALZENNA that was used before starting the P-gp inhibitor [see Drug Interactions (7.1)].

Monitor for increased adverse reactions and modify the dosage as recommended for adverse reactions when TALZENNA is coadministered with other P-gp inhibitors [see Dosage and Administration (2.5)].

3 DOSAGE FORMS AND STRENGTHS

Capsules: Each capsule is a liquid-filled soft-gelatin capsule with the following description.

Table 4. Dosage Forms and Strengths
Strength | Description
0.1 mg | Red oval capsule (printed with “TLZ” and “010”)
0.25 mg | Yellow oblong capsule (printed with “TLZ” and “025”)
0.35 mg | Pink oblong capsule (printed with “TLZ” and “035”)
0.5 mg | Pale orange oblong capsule (printed with “TLZ” and “050”)
0.75 mg | Red oblong capsule (printed with “TLZ” and “075”)
1 mg | Reddish brown oblong capsule (printed with “TLZ” and “1”)

4 CONTRAINDICATIONS

None.

5 WARNINGS AND PRECAUTIONS

5.1 Myelodysplastic Syndrome/Acute Myeloid Leukemia

Myelodysplastic Syndrome/Acute Myeloid Leukemia (MDS/AML), including cases with a fatal outcome, has been reported in patients who received TALZENNA.

Overall, MDS/AML has been reported in 0.4% (3 out of 788) of solid tumor patients treated with TALZENNA as a single agent in clinical studies. In TALAPRO-2, MDS/AML occurred in 2 out of 511 (0.4%) patients treated with TALZENNA and enzalutamide and in 0 out of 517 (0%) patients treated with placebo and enzalutamide [see Adverse Reactions (6.1)]. The durations of TALZENNA treatment in these 5 patients prior to developing MDS/AML were 0.3, 1, 2, 3, and 5 years. Most of these patients had received previous chemotherapy with platinum agents and/or other DNA damaging agents including radiotherapy.

Do not start TALZENNA until patients have adequately recovered from hematological toxicity caused by previous chemotherapy. Monitor blood counts monthly during treatment with TALZENNA. For prolonged hematological toxicities, interrupt TALZENNA and monitor blood counts weekly until recovery. If counts do not recover within 4 weeks, refer the patient to a hematologist for further investigations including bone marrow analysis and blood sample for cytogenetics. If MDS/AML is confirmed, discontinue TALZENNA.

5.2 Myelosuppression

Myelosuppression consisting of anemia, neutropenia, and/or thrombocytopenia, have been reported in patients treated with TALZENNA [see Adverse Reactions (6.1)].

Grade ≥3 anemia, neutropenia, and thrombocytopenia were reported, respectively, in 39%, 21%, and 15% of patients receiving TALZENNA as a single agent. Discontinuation due to anemia, neutropenia, and thrombocytopenia occurred, respectively, in 0.7%, 0.3%, and 0.3% of patients.

In TALAPRO-2, Grade ≥3 anemia, neutropenia, and thrombocytopenia were reported, respectively, in 48%, 19%, and 9% of patients receiving TALZENNA and enzalutamide. Forty-two percent of patients (216/511) required a red blood cell transfusion, including 25% (127/511) who required more than one transfusion. Discontinuation due to anemia, neutropenia, and thrombocytopenia occurred, respectively, in 8%, 3%, and 0.4% of patients.

Withhold TALZENNA until patients have adequately recovered from hematological toxicity caused by previous therapy. Monitor blood counts monthly during treatment with TALZENNA. If hematological toxicities do not resolve within 28 days, discontinue TALZENNA and refer the patient to a hematologist for further investigations including bone marrow analysis and blood sample for cytogenetics [see Dosage and Administration (2.5)].

5.3 Embryo-Fetal Toxicity

Based on its mechanism of action and findings from animal data, TALZENNA can cause fetal harm when administered to a pregnant woman. In an animal reproduction study, administration of talazoparib to pregnant rats during the period of organogenesis caused fetal malformations and structural skeletal variations, and embryo-fetal death at exposures that were 0.24 times the area under the concentration-time curve (AUC) in patients receiving the recommended human dose of 1 mg daily. Apprise pregnant women and females of reproductive potential of the potential risk to a fetus. Advise females of reproductive potential to use effective contraception during treatment and for 7 months following the last dose of TALZENNA [see Use in Specific Populations (8.1, 8.3), Clinical Pharmacology (12.1)].

Based on findings from genetic toxicity and animal reproduction studies, advise male patients with female partners of reproductive potential or who are pregnant to use effective contraception during treatment and for 4 months following the last dose of TALZENNA [see Use in Specific Populations (8.1, 8.3), Nonclinical Toxicology (13.1)].

6 ADVERSE REACTIONS

The following clinically significant adverse reactions are described elsewhere in the labeling:

- Myelodysplastic Syndrome/Acute Myeloid Leukemia [see Warnings and Precautions (5.1)]
- Myelosuppression [see Warnings and Precautions (5.2)]

6.1 Clinical Trials Experience

Because clinical trials are conducted under widely varying conditions, adverse reaction rates observed in the clinical trials of a drug cannot be directly compared to rates in the clinical trials of another drug and may not reflect the rates observed in practice.

The data described in the WARNINGS AND PRECAUTIONS section reflect exposure to single agent TALZENNA in solid tumor clinical studies, including 286 patients enrolled in EMBRACA trial and to TALZENNA 0.5 mg daily with enzalutamide in 511 patients enrolled in the TALAPRO-2 trial that included 197 patients with HRR gene-mutated mCRPC.

gBRCAm HER2-negative Locally Advanced or Metastatic Breast Cancer
EMBRACA
The safety of TALZENNA as a single agent was evaluated in gBRCAm patients with HER2-negative locally advanced or metastatic breast cancer who had previously received no more than 3 lines of chemotherapy for the treatment of locally advanced/metastatic disease [see Clinical Studies (14.1)]. EMBRACA was a randomized, open-label, multi-center study in which 412 patients received either TALZENNA 1 mg once daily (N=286) or a chemotherapy agent (capecitabine, eribulin, gemcitabine, or vinorelbine) of the healthcare provider's choice (N=126) until disease progression or unacceptable toxicity. The median duration of study treatment was 6.1 months in patients who received TALZENNA and 3.9 months in patients who received chemotherapy.

Serious adverse reactions of TALZENNA occurred in 32% of patients. Serious adverse reactions reported in >2% of patients included anemia (6%) and pyrexia (2%). Fatal adverse reactions occurred in 1% of patients, including cerebral hemorrhage, liver disorder, veno-occlusive liver disease, and worsening neurological symptoms (1 patient each).

Permanent discontinuation due to adverse reactions occurred in 5% of TALZENNA patients. Dosing interruptions due to an adverse reaction of any grade occurred in 65% of patients receiving TALZENNA; dose reductions due to any cause occurred in 53% of TALZENNA patients.

The most common (≥20%) adverse reactions, including laboratory abnormalities, were hemoglobin decreased, neutrophils decreased, lymphocytes decreased, platelets decreased, fatigue, glucose increased, aspartate aminotransferase increased, alkaline phosphatase increased, alanine aminotransferase increased, calcium decreased, nausea, headache, vomiting, alopecia, diarrhea, and decreased appetite.

Table 5 and Table 6 summarize the most common adverse reactions and laboratory abnormalities, respectively, in patients treated with TALZENNA or chemotherapy in the EMBRACA study.

Table 5. Adverse Reactions [Graded according to NCI CTCAE 4.03.] (≥20%) in Patients Receiving TALZENNA in EMBRACA
Adverse Reactions | TALZENNA; N=286 (%) |  |  | Chemotherapy; N=126 (%)
Adverse Reactions | Grades 1-4 | Grade 3 | Grade 4 | Grades 1-4 | Grade 3 | Grade 4
General Disorders and Administration Site Conditions
Fatigue [Includes fatigue and asthenia.] | 62 | 3 | 0 | 50 | 5 | 0
Gastrointestinal Disorders
Nausea | 49 | 0.3 | 0 | 47 | 2 | 0
Vomiting | 25 | 2 | 0 | 23 | 2 | 0
Diarrhea | 22 | 1 | 0 | 26 | 6 | 0
Nervous System Disorders
Headache | 33 | 2 | 0 | 22 | 1 | 0
Skin and Subcutaneous Tissue Disorders
Alopecia | 25 | 0 | 0 | 28 | 0 | 0
Metabolism and Nutrition Disorders
Decreased appetite | 21 | 0.3 | 0 | 22 | 1 | 0
Abbreviation: N=number of patients.

Clinically relevant adverse reactions in <20% of patients who received TALZENNA included abdominal pain (19%), dizziness (17%), dysgeusia (10%), dyspepsia (10%), stomatitis (8%), and febrile neutropenia (0.3%).

Table 6. Select Laboratory Abnormalities (≥25%) of Patients in EMBRACA
 | TALZENNA N [This number represents the safety population. The derived values in the table are based on the total number of evaluable patients for each laboratory parameter.] =286 (%) |  |  | Chemotherapy N=126 (%)
Parameter | Grades 1-4 | Grade 3 | Grade 4 | Grades 1-4 | Grade 3 | Grade 4
Hemoglobin decreased | 90 | 39 | 0 | 77 | 6 | 0
Neutrophils decreased | 68 | 17 | 3 | 70 | 21 | 17
Lymphocytes decreased | 76 | 17 | 0.7 | 53 | 8 | 0.8
Platelets decreased | 55 | 11 | 4 | 29 | 2 | 0
Glucose increased [This number represents non-fasting glucose.] | 54 | 2 | 0 | 51 | 2 | 0
Aspartate aminotransferase increased | 37 | 2 | 0 | 48 | 3 | 0
Alkaline phosphatase increased | 36 | 2 | 0 | 34 | 2 | 0
Alanine aminotransferase increased | 33 | 1 | 0 | 37 | 2 | 0
Calcium decreased | 28 | 1 | 0 | 16 | 0 | 0
Abbreviation: N=number of patients.

HRR Gene-mutated mCRPC

The safety of TALZENNA with enzalutamide was evaluated in patients with HRR gene-mutated mCRPC enrolled in TALAPRO-2 [see Clinical Studies (14.2)]. Patients were randomized to receive either TALZENNA 0.5 mg with enzalutamide 160 mg once daily (N=197), or placebo with enzalutamide 160 mg once daily (N=199) until disease progression or unacceptable toxicity. Among patients receiving TALZENNA, 86% were exposed for 6 months or longer, 60% were exposed for greater than one year, and 18% were exposed for greater than two years.

Serious adverse reactions of TALZENNA with enzalutamide occurred in 30% of patients. Serious adverse reactions reported in >2% of patients included anemia (9%) and fracture (3%). Fatal adverse reactions occurred in 1.5% of patients, including pneumonia, COVID infection, and sepsis (1 patient each).

Permanent discontinuation of TALZENNA due to adverse reactions occurred in 10% of patients treated in the TALZENNA with enzalutamide arm. The most common adverse reactions which resulted in permanent discontinuation of TALZENNA were anemia (4%), fatigue, bone fracture, ischemic heart disease, and spinal cord compression (1% each).

Dosage interruption of TALZENNA due to adverse reactions occurred in 58% of patients treated in the TALZENNA with enzalutamide arm. The most common adverse reactions which resulted in dose interruption of TALZENNA were anemia (42%), neutropenia (15%), and platelet count decreased (9%) and fatigue (5%).

Dose reduction of TALZENNA due to adverse reactions occurred in 52% of patients treated in the TALZENNA with enzalutamide arm. The most common adverse reactions which resulted in dose reduction of TALZENNA were anemia (43%), neutrophil count decreased (15%), platelet count decreased (6%), and fatigue (4%).

The most common adverse reactions (≥10%), including laboratory abnormalities, in patients who received TALZENNA with enzalutamide were hemoglobin decreased, neutrophils decreased, lymphocytes decreased, fatigue, platelets decreased, calcium decreased, nausea, decreased appetite, sodium decreased, phosphate decreased, fractures, magnesium decreased, dizziness, bilirubin increased, potassium decreased, and dysgeusia.

Table 7 and Table 8 summarize the most common adverse reactions and laboratory abnormalities, respectively, in the TALAPRO-2 study.

Table 7. Adverse Reactions [Graded according to NCI CTCAE 4.03.] (≥10%) in Patients Receiving TALZENNA (with a Difference Between Arms of ≥2%) in TALAPRO-2
 | TALZENNA with Enzalutamide; N=197 |  |  | Placebo with Enzalutamide; N=199
 | Grades 1-4; % | Grade 3; % | Grade 4; % | Grades 1-4; % | Grade 3; % | Grade 4; %
Fatigue [Includes fatigue and asthenia.] | 49 | 4 | 0 | 40 | 1 | 0
Nausea | 21 | 2 | 0 | 17 | 1 | 0.5
Decreased appetite | 20 | 1 | 0 | 14 | 1 | 1
Fractures [Fractures include multiple similar terms.] | 14 | 3 | 0 | 10 | 1.5 | 0
Dizziness [Includes dizziness, dizziness postural, vertigo.] | 13 | 1.5 | 0 | 9 | 1.5 | 0
Dysgeusia [Includes ageusia, anosmia, dysgeusia.] | 10 | 0 | 0 | 4.5 | 0 | 0
Abbreviation: N=number of patients.

Clinically relevant adverse reactions in <10% of patients who received TALZENNA with enzalutamide included abdominal pain (9%), vomiting (9%), alopecia (7%), dyspepsia (4%), venous thromboembolism (3%) and stomatitis (2%).

Table 8. Select Laboratory Abnormalities (≥10%) That Worsened from Baseline in Patients Who Received TALZENNA in TALAPRO-2
Laboratory Abnormality | TALZENNA with Enzalutamide; N=197 [The denominator used to calculate the rate varied from 198 to 199 in the placebo with enzalutamide arm based on the number of patients with a baseline value and at least one post-treatment value.] |  |  | Placebo with Enzalutamide; N=199
Laboratory Abnormality | Grades 1‑4; % | Grade 3; % | Grade 4; % | Grades 1‑4; % | Grade 3; % | Grade 4; %
Hemoglobin decreased | 79 | 41 | 0 | 34 | 6 | 0
Neutrophils decreased | 60 | 18 | 1 | 18 | 0 | 1
Lymphocytes decreased | 58 | 13 | 0 | 36 | 7 | 0
Platelets decreased | 45 | 6 | 3 | 8 | 0.5 | 0
Calcium decreased | 25 | 0 | 1 | 11 | 0 | 1
Sodium decreased | 22 | 3 | 0 | 20 | 1.5 | 0
Phosphate decreased | 17 | 3 | 1 | 13 | 2 | 0
Magnesium decreased | 14 | 0 | 1 | 12 | 0 | 0.5
Bilirubin increased | 11 | 0.5 | 0 | 7 | 0 | 0
Potassium decreased | 11 | 0 | 1 | 7 | 1 | 0.5
Abbreviation: N=number of patients.

7 DRUG INTERACTIONS

7.1 Effect of Other Drugs on TALZENNA

Effect of P-gp Inhibitors

Breast Cancer

Avoid coadministration of TALZENNA with the following P-gp inhibitors: itraconazole, amiodarone, carvedilol, clarithromycin, itraconazole, and verapamil. If coadministration of TALZENNA with these P-gp inhibitors cannot be avoided, reduce the dose of TALZENNA [see Dosage and Administration (2.7)]. When the P-gp inhibitor is discontinued, increase the dose of TALZENNA [see Dosage and Administration (2.7)].

Coadministration of TALZENNA with these P-gp inhibitors increased talazoparib concentrations [see Clinical Pharmacology (12.3)], which may increase the risk of adverse reactions.

Monitor for increased adverse reactions and modify the dosage as recommended for adverse reactions when TALZENNA is coadministered with other P-gp inhibitors [see Dosage and Administration (2.5)].

HRR Gene-mutated mCRPC

The effect of coadministration of P-gp inhibitors on talazoparib exposure when TALZENNA is taken with enzalutamide has not been studied. Monitor patients for increased adverse reactions and modify the dosage as recommended for adverse reactions when TALZENNA is coadministered with a P-gp inhibitor [see Dosage and Administration (2.5)].

Effect of Breast Cancer Resistance Protein (BCRP) Inhibitors

Monitor patients for increased adverse reactions and modify the dosage as recommended for adverse reactions when TALZENNA is coadministered with a BCRP inhibitor [see Dosage and Administration (2.5)].

Coadministration of TALZENNA with BCRP inhibitors may increase talazoparib exposure [see Clinical Pharmacology (12.3)], which may increase the risk of adverse reactions.

8 USE IN SPECIFIC POPULATIONS

8.1 Pregnancy

Risk Summary

Based on findings from animal studies and its mechanism of action [see Clinical Pharmacology (12.1)], TALZENNA can cause embryo-fetal harm when administered to a pregnant woman. There are no available data on TALZENNA use in pregnant women to inform a drug-associated risk. In an animal reproduction study, the administration of talazoparib to pregnant rats during the period of organogenesis caused fetal malformations and structural skeletal variations and embryo-fetal death at maternal exposures that were 0.24 times the AUC in patients receiving the recommended dose of 1 mg daily (see Data). Apprise pregnant women and females of reproductive potential of the potential risk to a fetus.

The background risk of major birth defects and miscarriage for the indicated population is unknown. In the general U.S. population, the estimated background risks of major birth defects and miscarriage in clinically recognized pregnancies are 2% to 4% and 15% to 20%, respectively.

Data

Animal Data

In an embryo-fetal development toxicity study, pregnant rats received oral doses of 0.015, 0.05, and 0.15 mg/kg/day talazoparib during the period of organogenesis. Talazoparib caused embryo-fetal death at doses ≥0.015 mg/kg/day (approximately 0.24 times the AUC in patients at the recommended dose of 1 mg daily). A dose of 0.015 mg/kg/day caused decreased fetal body weights and an increased incidence of fetal malformations (depressed eye bulge, small eye, split sternebra, and fused cervical vertebral arch) and structural variations including misshapen or incomplete ossification of the sternebra, skull, rib, and vertebra.

8.2 Lactation

Risk Summary

There are no data on the presence of talazoparib in human milk, the effects of the drug on milk production, or the effects of the drug on the breastfed child. Because of the potential for serious adverse reactions in a breastfed child from talazoparib, advise lactating women not to breastfeed during treatment with TALZENNA and for 1 month after the last dose.

8.3 Females and Males of Reproductive Potential

TALZENNA can cause fetal harm when administered to pregnant women [see Use in Specific Populations (8.1)].

Pregnancy Testing
Verify pregnancy status in females of reproductive potential prior to initiating TALZENNA treatment.

Contraception
Females
Advise females of reproductive potential to use effective contraception during treatment and for 7 months following the last dose of TALZENNA.

Males
Based on genotoxicity and animal reproduction studies, advise male patients with female partners of reproductive potential and pregnant partners to use effective contraception during treatment with TALZENNA and for 4 months following the last dose [see Use in Specific Populations (8.1), Nonclinical Toxicology (13.1)].

Infertility
Males
Based on animal studies, TALZENNA may impair fertility in males of reproductive potential [see Nonclinical Toxicology (13.1)].

8.4 Pediatric Use

The safety and effectiveness of TALZENNA have not been established in pediatric patients.

8.5 Geriatric Use

In clinical trials of TALZENNA enrolling 494 patients with advanced solid tumors who received TALZENNA 1 mg daily as a single agent, 85 (17%) patients were ≥65 years of age, and this included 19 (4%) patients who were ≥75 years old. There were 5 patients ≥85 years old. In the TALAPRO-2 trial, of 197 patients who received TALZENNA, 77% were ≥65 years of age, while 30% were ≥75 years of age. No overall differences in safety or effectiveness of TALZENNA were observed between these patients and younger patients.

8.6 Hepatic Impairment

No dosage modification is recommended for patients with hepatic impairment [see Clinical Pharmacology (12.3)].

8.7 Renal Impairment

Reduce the recommended dosage of TALZENNA in patients with moderate (CLcr 30 – 59 mL/min) and severe (CLcr 15 – 29 mL/min) renal impairment [see Dosage and Administration (2.7)]. Monitor patients with severe renal impairment for increased adverse reactions and modify the dosage as recommended for adverse reactions [see Dosage and Administration (2.5)].

No dose adjustment is recommended for patients with mild renal impairment (CLcr 60 – 89 mL/min). TALZENNA has not been studied in patients requiring hemodialysis.

11 DESCRIPTION

Talazoparib is an inhibitor of mammalian polyadenosine 5'-diphosphoribose (ADP-ribose) polymerase (PARP) enzymes. TALZENNA contains talazoparib tosylate. The chemical name of talazoparib tosylate is (8S,9R)-5-Fluoro-8-(4-fluorophenyl)-9-(1-methyl-1H-1,2,4-triazol-5-yl)-2,7,8,9-tetrahydro-3H-pyrido[4,3,2-de]phthalazin-3-one 4-methylbenzenesulfonate (1:1). The chemical formula of talazoparib tosylate is C26H22F2N6O4S, and the relative molecular mass is 552.56 Daltons. The chemical structure of talazoparib tosylate is shown below:

Talazoparib tosylate is a white to yellow solid. TALZENNA capsules for oral use are available as liquid-filled soft gelatin capsules. Each capsule contains 0.1 mg, 0.25 mg, 0.35 mg, 0.5 mg, 0.75, or 1 mg of talazoparib equivalent to 0.145 mg, 0.363 mg, 0.509 mg, 0.727 mg, 1.09 mg, or 1.453 mg talazoparib tosylate, respectively.

TALZENNA capsules contain the following inactive ingredients: gelatin, glycerol, iron oxide (red), iron oxide (yellow), polyethylene glycol 400, purified water, sorbitol, titanium dioxide, and tocopherol.

12 CLINICAL PHARMACOLOGY

12.1 Mechanism of Action

Talazoparib is an inhibitor of PARP enzymes, including PARP1 and PARP2, which play a role in DNA repair. In vitro studies with cancer cell lines that harbored defects in DNA repair genes, including BRCA1 and BRCA2, have shown that talazoparib-induced cytotoxicity may involve inhibition of PARP enzymatic activity and increased formation of PARP-DNA complexes resulting in DNA damage, decreased cell proliferation, and apoptosis. Talazoparib anti-tumor activity was observed in patient-derived xenograft breast cancer models bearing mutated BRCA1 or mutated BRCA2 or wild type BRCA1 and BRCA2.

12.2 Pharmacodynamics

The exposure-response relationship and time course of pharmacodynamic response for the safety and effectiveness of TALZENNA have not been fully characterized.

Cardiac Electrophysiology

At a dose of 1 mg (the recommended dosage for treatment of breast cancer), TALZENNA had no large QTc prolongation (i.e., >20 ms).

12.3 Pharmacokinetics

After administration of TALZENNA 1 mg orally once daily as a single agent (the recommended dosage for breast cancer), the mean [% coefficient of variation (CV%)] AUC and maximum observed plasma concentration (Cmax) of talazoparib at steady-state was 173 (32%) ng.hr/mL and 19 (32%) ng/mL, respectively. The mean (CV%) steady-state Ctrough was 3.5 (61%) ng/mL.

After administration of TALZENNA 0.5 mg orally once daily (the recommended dosage for prostate cancer) with enzalutamide, the mean (CV%) steady-state Ctrough ranged from 3.3 to 3.7 ng/mL (45% to 48%).

The pharmacokinetics (PK) of talazoparib is linear from 0.025 mg to 2 mg (2 times the recommended dose for breast cancer). The median accumulation ratio of talazoparib following 1 mg orally once daily is 2.3 to 5.2. Talazoparib plasma concentrations reached steady-state within 2 to 3 weeks when administered as a single agent and within 9 weeks when coadministered with enzalutamide.

Absorption
The median time to Cmax (Tmax) was approximately 1 hour (range: 0.4 to 4 hours) after dosing.

Food Effect
Following administration of a TALZENNA 1 mg dose soft gelatin capsule with high-fat, high-calorie food (approximately 800 to 1,000 calories with 150, 250, and 500 to 600 calories from protein, carbohydrate, and fat, respectively), the mean steady-state Cmax was decreased by 42%, the median Tmax was delayed from 1 to 4 hours, and AUC was not affected as compared to those under fasted conditions.

Distribution
The mean apparent volume of distribution of talazoparib is 420 L. In vitro, protein binding of talazoparib is 74% and is independent of talazoparib concentration.

Elimination
The mean terminal plasma half-life (±standard deviation) is 90 (±58) hours and the mean apparent oral clearance (inter-subject variability) is 6.5 L/h (31%).

Metabolism
Talazoparib undergoes minimal hepatic metabolism. The identified metabolic pathways include mono-oxidation, dehydrogenation, cysteine conjugation of mono-desfluoro-talazoparib, and glucuronide conjugation.

Excretion
Excretion of talazoparib in urine was the major route of elimination. Approximately 69% (55% unchanged) of the total administered radiolabeled dose of talazoparib was recovered in urine, and 20% (14% unchanged) was recovered in feces.

Specific Populations
Age (18 to 88 years), sex, race (361 White, 41 Asian, 16 Black, 9 Others, and 63 Not Reported), body weight (36 to 162 kg), and mild to severe hepatic impairment had no clinically significant effect on the PK of talazoparib.

Patients with Renal Impairment
Mild (eGFR 60 – 89 mL/min/1.73 m^2) renal impairment had no clinically significant effect on talazoparib pharmacokinetics. Talazoparib steady-state total exposure (AUC) increased by 43% in subjects with moderate (eGFR 30 – 59 mL/min/1.73 m^2) renal impairment and 163% in patients with severe (eGFR 15 – 29 mL/min/1.73 m^2) renal impairment relative to subjects with normal renal function (eGFR ≥ 90 mL/min/1.73 m^2). Talazoparib steady-state peak concentration (Cmax) increased by 32% in subjects with moderate renal impairment and 89% in subjects with severe renal impairment, relative to subjects with normal renal function. Similar increases in AUC were observed with talazoparib when given with enzalutamide for patients with moderate and severe renal impairment. The PK of talazoparib has not been studied in patients requiring hemodialysis. There was no evidence of a relationship between the protein binding of talazoparib and renal function.

Drug Interaction Studies
Clinical Studies
Effect of P-gp Inhibitors: Coadministration of a P-gp inhibitor (itraconazole) with a single 0.5 mg dose of TALZENNA increased talazoparib AUC and Cmax by approximately 56% and 40%, respectively. Coadministration with the following other P-gp inhibitors: amiodarone, carvedilol, clarithromycin, itraconazole, and verapamil increased talazoparib exposure by 45%.

Coadministration with other P-gp inhibitors (including azithromycin, atorvastatin, diltiazem, felodipine, fluvoxamine, and quercetin) had no clinically significant effect on talazoparib pharmacokinetics.

Effect of P-gp Inducers: Coadministration of a P-gp inducer (rifampin) with a single 1 mg dose of TALZENNA increased talazoparib Cmax by 37% with no effect on talazoparib AUC.

Effect of Acid-Reducing Agents: Coadministration of acid-reducing agents including proton pump inhibitors (PPI), histamine receptor 2 antagonists (H2RA), or other acid-reducing agents has no effect on the absorption of talazoparib.

Enzalutamide: Coadministration of enzalutamide with TALZENNA increased talazoparib exposure approximately 2-fold.

In Vitro Studies
Transporters: Talazoparib is a substrate of P-gp and BCRP transporters, but not a substrate of OATP1B1, OATP1B3, OCT1, OCT2, OAT1, OAT3, BSEP, MATE1, or MATE2-K.

Talazoparib is not an inhibitor of P-gp, BCRP, OATP1B1, OATP1B3, OCT1, OCT2, OAT1, OAT3, BSEP, MATE1, or MATE2-K.

CYP Enzymes: Talazoparib is not an inhibitor of CYP1A2, CYP2B6, CYP2C8, CYP2C9, CYP2C19, CYP2D6, or CYP3A4/5.

Talazoparib is not an inducer of CYP1A2, CYP2B6, or CYP3A4.

UGT: Talazoparib is not an inhibitor of UGT isoforms (1A1, 1A4, 1A6, 1A9, 2B7, and 2B15).

13 NONCLINICAL TOXICOLOGY

13.1 Carcinogenesis, Mutagenesis, Impairment of Fertility

Carcinogenicity studies have not been conducted with talazoparib.

Talazoparib was clastogenic in an in vitro chromosomal aberration assay in human peripheral blood lymphocytes and in an in vivo bone marrow micronucleus assay in rats. This clastogenicity is consistent with genomic instability resulting from the primary pharmacology of talazoparib, indicating the potential for genotoxicity in humans. Talazoparib was not mutagenic in a bacterial reverse mutation (Ames) test.

Fertility studies in animals have not been conducted with talazoparib. In repeat-dose toxicity studies up to 3-months duration, talazoparib-related findings in the testis and epididymis at doses ≥0.04 mg/kg/day in rats and ≥0.01 mg/kg/day in dogs included decreased organ weights, luminal cellular debris, reduced sperm, and degeneration/atrophy. These doses in rats and dogs resulted in approximately 1.0 times and 0.2 times, respectively, the exposure (AUC) in humans at the recommended dose of 1 mg daily. Follicular atresia of the ovary was observed in rats at doses ≥1 mg/kg/day talazoparib, approximately 9.5 times the AUC in patients at the recommended dose of 1 mg daily.

14 CLINICAL STUDIES

14.1 Deleterious or Suspected Deleterious Germline BRCA-mutated HER2-negative Locally Advanced or Metastatic Breast Cancer

EMBRACA (NCT01945775) was an open-label study in which patients (N=431) with gBRCAm HER2-negative locally advanced or metastatic breast cancer were randomized 2:1 to receive TALZENNA 1 mg or healthcare provider's choice of chemotherapy (capecitabine, eribulin, gemcitabine, or vinorelbine) until disease progression or unacceptable toxicity. Randomization was stratified by prior lines of chemotherapy for metastatic disease (0 versus 1, 2, or 3), by triple-negative disease status [triple-negative breast cancer (TNBC) versus non-TNBC], and history of central nervous system (CNS) metastasis (yes versus no).

Patients received no more than 3 prior cytotoxic chemotherapy regimens for their metastatic or locally advanced disease. Patients were required to have received treatment with an anthracycline and/or a taxane (unless contraindicated) in the neoadjuvant, adjuvant, and/or metastatic treatment setting. First-line treatment for advanced or metastatic disease with no prior adjuvant chemotherapy was allowed if the investigator determined that 1 of the 4 chemotherapy choices in the control arm would be an appropriate treatment option for the patient. Patients with prior platinum therapy for advanced disease were required to have no evidence of disease progression during platinum therapy. No prior treatment with a PARP inhibitor was permitted. Of the 431 patients randomized in the EMBRACA study, 408 (95%) were centrally confirmed to have a deleterious or suspected deleterious gBRCAm using a clinical trial assay; out of which 354 (82%) were confirmed using the BRACAnalysis CDx®. BRCA mutation status [breast cancer susceptibility gene 1 (BRCA1)-positive or breast cancer susceptibility gene 2 (BRCA2)-positive] was similar across both treatment arms.

The median age of patients treated with TALZENNA was 46 years (range 28 to 84) and 51 years (range 24 to 89) among patients treated with chemotherapy. Among all randomized patients, 1% versus 2% were males, 67% versus 75% were White; 11% versus 11% were Asian, and 4% versus 1% were Black or African American in the TALZENNA and chemotherapy arms, respectively. Almost all patients (98%) in both arms had an Eastern Cooperative Oncology Group (ECOG) performance status of 0 or 1. Approximately 56% of patients had estrogen receptor-positive and/or progesterone receptor-positive disease; 44% of patients had triple-negative disease, and the proportions were balanced across both treatment arms. Fifteen percent (15%) of patients in the TALZENNA arm and 14% of patients in the chemotherapy arm had a history of CNS metastases. Ninety-one percent (91%) of patients in the TALZENNA arm had received prior taxane therapy, and 85% had received prior anthracycline therapy in any setting. Sixteen percent (16%) of patients in the TALZENNA arm and 21% of patients in the chemotherapy arm had received prior platinum treatment in any setting. The median number of prior cytotoxic regimens for patients with advanced breast cancer was one; 38% received no prior cytotoxic regimens for advanced or metastatic disease, 37% received one, 20% received two, and 5% received three or more prior cytotoxic regimens.

The major efficacy outcome measure was progression-free survival (PFS) evaluated according to Response Evaluation Criteria in Solid Tumors (RECIST) version 1.1, as assessed by blinded independent central review (BICR). A statistically significant improvement in PFS was demonstrated for TALZENNA compared to chemotherapy. A sensitivity analysis of investigator-assessed PFS was consistent with the BICR-assessed PFS results. Consistent PFS results were observed across patient subgroups defined by study stratification factors (prior lines of chemotherapy, TNBC status, and history of CNS metastases). Efficacy data from the EMBRACA study are summarized in Table 9, and the Kaplan-Meier curves for PFS are shown in Figure 1 and final overall survival (OS) in Figure 2.

Table 9. Efficacy Results – EMBRACA Study
 | TALZENNA | Chemotherapy
PFS by BICR | N=287 | N=144
Disease progression or deaths, n (%) | 186 (65) | 83 (58)
Median months (95% CI) | 8.6 (7.2, 9.3) | 5.6 (4.2, 6.7)
Hazard ratio (95% CI) [Hazard ratio is estimated from a Cox proportional hazards model stratified by prior use of chemotherapy for metastatic disease (0 versus 1, 2, or 3), by triple-negative disease status [triple-negative breast cancer (TNBC) versus non TNBC], and by history of central nervous system metastasis (yes versus no) and is relative to overall chemotherapy with <1 favoring talazoparib.] | 0.54 (0.41, 0.71)
p-value [p-values (2-sided) from the log-rank test stratified by number of prior cytotoxic chemotherapy regimens, triple-negative status and history of central nervous system metastasis.] | p<0.0001
Patients with Measurable Disease by Investigator [Conducted in ITT population with measurable disease at baseline.] | N=219 | N=114
ORR, % (95% CI) [Response rate based on confirmed responses.] | 50.2 (43.4, 57.0) | 18.4 (11.8, 26.8)
Median [Median estimated from Kaplan-Meier probabilities.] DOR months (95% CI) | 6.4 (5.4, 9.5) | 3.9 (3.0, 7.6)
OS | N=287 | N=144
Deaths, n (%) | 216 (75) | 108 (75)
Median months (95% CI) | 19.3 (16.6, 22.5) | 19.5 (17.4, 22.4)
Hazard ratio (95% CI) | 0.85 (0.67, 1.07)
p-value | p=0.1693
Abbreviations: BICR=blinded independent central review; CI=confidence interval; DOR=duration of response; ITT=intent-to-treat; N=number of patients; ORR=objective response rate; OS=overall survival; PFS=progression-free survival.

Figure 1. Kaplan-Meier Curves of PFS – EMBRACA Study

Abbreviation: PFS=progression-free survival.

Figure 2. Kaplan-Meier Curves of OS – EMBRACA Study (ITT Population)

Abbreviations: ITT=intent-to-treat; OS=overall survival.

14.2 HRR Gene-mutated mCRPC

The efficacy of TALZENNA with enzalutamide was evaluated in TALAPRO-2 (NCT03395197), a randomized, double-blind, placebo-controlled, multi-cohort trial in which 399 patients with HRR gene-mutated (HRRm) mCRPC were randomized 1:1 to receive enzalutamide 160 mg daily plus either TALZENNA 0.5 mg or placebo daily until unacceptable toxicity or disease progression. Mutation status of HRR genes was determined prospectively using solid tumor tissue or circulating tumor DNA (ctDNA)-based next generation sequencing assays. Patients were required to have a mutation in at least one of 12 genes involved directly or indirectly in the HRR pathway (ATM, ATR, BRCA1, BRCA2, CDK12, CHEK2, FANCA, MLH1, MRE11A, NBN, PALB2, or RAD51C). All patients received a GnRH analog or had prior bilateral orchiectomy and needed to have progressed on prior androgen deprivation therapy. Prior treatment with a CYP17 inhibitor or docetaxel for metastatic castration-sensitive prostate cancer (mCSPC) was permitted. Randomization was stratified by previous treatment with a CYP17 inhibitor or docetaxel (yes/no).

The median age was 70 years (range: 41 to 90); 100% were male; 68% were White, 21% Asian, 2.8% Black, 0.8% Other, 7% unknown/not reported; 12% were Hispanic/Latino; and baseline ECOG performance status was 0 (62%) or 1 (38%). Thirty-nine percent of patients had bone-only disease; 15% had visceral disease. In the mCSPC setting, 29% percent of patients had received docetaxel and 9% had received a prior CYP17 inhibitor. The most commonly mutated HRR genes (>5%), including co-occurring mutations, were: BRCA2 (34%), ATM (22%), CDK12 (19%), CHEK2 (18%), and BRCA1 (6%).

The major efficacy outcome measure was radiographic progression-free survival (rPFS) evaluated according to RECIST, version 1.1 and Prostate Cancer Working Group (PCWG3) (bone) criteria, assessed by BICR. An additional efficacy outcome measure was OS.

A statistically significant improvement in rPFS and OS were demonstrated in patients randomized to TALZENNA with enzalutamide compared with placebo with enzalutamide. Efficacy results are presented in Table 10, and Figures 3 and 4.

Table 10. Efficacy Results – TALAPRO-2 (HRR Gene-mutated mCRPC)
 | TALZENNA with Enzalutamide; N=200 |  | Placebo with Enzalutamide; N=199
Radiographic Progression-free Survival (rPFS) by BICR
Number of events, n (%) | 66 (33) |  | 104 (52)
Median months (95% CI) | NR (21.9, NR) |  | 13.8 (11.0, 16.7)
Hazard ratio (95% CI) [Hazard ratio and CI are based on Cox PH model stratified by previous treatment for CSPC.] | 0.45 (0.33, 0.61)
p-value [p-value (2-sided) is based on log-rank test stratified by previous treatment for CSPC.] | p<0.0001
Overall Survival (OS)
Deaths, n (%) | 93 (47) | 126 (63)
Median months (95% CI) | 45.1 (35.4, NR) | 31.1 (27.3, 35.4)
Hazard ratio (95% CI) | 0.62 (0.48, 0.81)
p-value | p=0.0005
Abbreviations: BICR=blinded independent central review; CI=confidence interval; CSPC=castration-sensitive prostate cancer; HRR=homologous recombination repair; mCRPC=metastatic castration-resistant prostate cancer; N=number of patients; NR=not reached.

Figure 3. Kaplan-Meier Curves of rPFS - TALAPRO-2 (HRR Gene-mutated mCRPC)

Abbreviations: HRR=homologous recombination repair; mCRPC=metastatic castration-resistant prostate cancer; rPFS=radiographic progression-free survival.

Figure 4. Kaplan-Meier Curves of OS – TALAPRO-2 (HRR Gene-mutated mCRPC)

Abbreviations: HRR=homologous recombination repair; mCRPC=metastatic castration-resistant prostate cancer; OS=overall survival.

Exploratory subgroup analyses of rPFS and OS for patients with BRCA-mutated (BRCAm) and non-BRCAm HRRm are presented in Table 11.

Table 11. Exploratory rPFS and OS Subgroup Analyses by BRCAm Status for TALAPRO-2 (HRR Gene-mutated mCRPC)
 | BRCAm |  | Non-BRCAm HRRm [Includes 4 patients who were incorrectly randomized in the HRRm stratum who did not have HRR gene mutations.]
 | TALZENNA with Enzalutamide; N=71 | Placebo with Enzalutamide; N=84 | TALZENNA with Enzalutamide; N=129 | Placebo with Enzalutamide; N=115
rPFS
Number of events, n (%) | 15 (21) | 54 (64) | 51 (40) | 50 (43)
Median months (95% CI) | NR (NR, NR) | 11.0 (8.3, 11.1) | 24.7 (16.4, NR) | 16.7 (13.8, 27.7)
Hazard ratio (95% CI) | 0.20 (0.11, 0.36) |  | 0.74 (0.50, 1.09)
Overall Survival (OS)
Deaths, n (%) | 30 (42) | 56 (67) | 63 (49) | 70 (61)
Median months (95% CI) | NR; (35.4, NR) | 28.5; (24.5, 34.4) | 42.4; (34.2, NR) | 32.6; (28.0, 42.2)
Hazard ratio (95% CI) [Hazard ratio and CI are based on Cox PH model unstratified by previous treatment for CSPC.] | 0.48 (0.31, 0.75) |  | 0.71 (0.51, 1.00)
Abbreviations: BRCAm=breast cancer susceptibility gene-mutated; CI=confidence interval; CSPC=castration-sensitive prostate cancer; HRRm=homologous recombination repair gene-mutated; NR=not reached; rPFS=radiographic progression-free survival.

16 HOW SUPPLIED/STORAGE AND HANDLING

TALZENNA is supplied in strengths and package configurations as described in Table 12:

Table 12. TALZENNA Capsules
Package Configuration | Capsule Strength (mg) | NDC | Print
Bottles of 30 capsules | 0.1 | 0069-0252-30 | Red oval liquid-filled soft gelatin capsule printed with “TLZ” and “010”.
Bottles of 30 capsules | 0.25 | 0069-0353-30 | Yellow oblong liquid-filled soft gelatin capsule printed with “TLZ” and “025”.
Bottles of 30 capsules | 0.35 | 0069-0454-30 | Pink oblong liquid-filled soft gelatin capsule printed with “TLZ” and “035”.
Bottles of 30 capsules | 0.5 | 0069-0546-30 | Pale orange oblong liquid-filled soft gelatin capsule printed with “TLZ” and “050”.
Bottles of 30 capsules | 0.75 | 0069-0655-30 | Red oblong liquid-filled soft gelatin capsule printed with “TLZ” and “075”.
Bottles of 30 capsules | 1 | 0069-0757-30 | Reddish brown oblong liquid-filled soft gelatin capsule printed with “TLZ” and “1”.

Storage

Store at 20°C to 25°C (68°F to 77°F); excursions permitted between 15°C to 30°C (59°F to 86°F). [See USP Controlled Room Temperature].

17 PATIENT COUNSELING INFORMATION

Advise the patient to read the FDA-approved patient labeling (Patient Information).

- MDS/AML: Advise patients to contact their healthcare provider if they experience weakness, feeling tired, fever, weight loss, frequent infections, bruising, bleeding easily, breathlessness, blood in urine or stool, and/or laboratory findings of low blood cell counts, or a need for blood transfusions. This may be a sign of hematological toxicity or a more serious uncommon bone marrow problem called MDS or AML, which have been reported in patients who received PARP inhibitors [see Warnings and Precautions (5.1)].
- Myelosuppression: Advise patients that TALZENNA may affect hematopoiesis and can cause anemia, leukopenia/neutropenia, and/or thrombocytopenia [see Warnings and Precautions (5.2)].
- Administration Instructions: Advise patients that TALZENNA can be taken once daily with or without food. Instruct patients that if they miss a dose of TALZENNA, they should take their next normal dose at the usual time. Also advise patients to swallow each capsule whole, and that capsules must not be opened or dissolved [see Dosage and Administration (2.4)].
- Embryo-Fetal Toxicity: Advise females to inform their healthcare provider if they are pregnant or become pregnant. Inform female patients of the risk to a fetus and potential loss of the pregnancy [see Use in Specific Populations (8.1)]. Advise females of reproductive potential to use effective contraception during treatment with TALZENNA and for 7 months after the last dose. Advise male patients with female partners of reproductive potential or who are pregnant to use effective contraception during treatment and for 4 months after receiving the last dose of TALZENNA [see Warnings and Precautions (5.3), Use in Specific Populations (8.1, 8.3)].
- Lactation: Advise patients not to breastfeed while taking TALZENNA and for 1 month after receiving the last dose [see Use in Specific Populations (8.2)].

This product's labeling may have been updated. For the most recent prescribing information, please visit http://www.pfizer.com.

LAB-1561-2.0

PATIENT INFORMATION
TALZENNA® (Tal-ZEN-ah)
(talazoparib)
capsules

What is the most important information I should know about TALZENNA?
TALZENNA may cause serious side effects, including:

- Bone marrow problems called Myelodysplastic Syndrome (MDS) or Acute Myeloid Leukemia (AML). Some people who have cancer and who have received previous treatment with chemotherapy or certain other medicines for their cancer have developed MDS or AML during or after treatment with TALZENNA. MDS or AML may lead to death. If you develop MDS or AML, your healthcare provider will stop treatment with TALZENNA.
  Symptoms of low blood cell counts are common during treatment with TALZENNA, but can be a sign of serious problems, including MDS or AML. Tell your healthcare provider if you have any of the following symptoms during treatment with TALZENNA:

○ weakness

○ weight loss

○ fever

○ frequent infections

○ blood in urine or stool

○ shortness of breath

○ feeling very tired

○ bruising or bleeding more easily

Your healthcare provider will do blood tests to check your blood cell counts:

○ every month during treatment with TALZENNA.

○ weekly if you have low blood cell counts that last a long time.

Your healthcare provider may change your dose, temporarily stop, or permanently stop treatment with TALZENNA if you get certain side effects.

See “What are the possible side effects of TALZENNA?” below for other side effects of TALZENNA.

What is TALZENNA?
TALZENNA is a prescription medicine used:

- alone to treat adults with human epidermal growth factor receptor 2 (HER2)-negative breast cancer:
  - who have a certain type of an abnormal inherited BRCA gene, and
  - whose cancer has spread to other parts of the body (locally advanced or metastatic).
Your healthcare provider will perform a test to make sure that TALZENNA is right for you.
- in combination with a medicine called enzalutamide, to treat adults with prostate cancer
  - with certain abnormal inherited or acquired genes called homologous recombination repair (HRR genes) and
  - which no longer responds to hormone therapy or surgical treatment to lower testosterone and has spread to other parts of the body (metastatic).
Your healthcare provider will perform a test to make sure that TALZENNA is right for you.

It is not known if TALZENNA is safe and effective in children.

Before taking TALZENNA, tell your healthcare provider about all of your medical conditions, including if you:

- have kidney problems.
- are pregnant or plan to become pregnant. TALZENNA can harm your unborn baby and may cause loss of pregnancy (miscarriage). You should not become pregnant during treatment with TALZENNA.
Females who are able to become pregnant:
  1. Your healthcare provider may do a pregnancy test before you start treatment with TALZENNA.
  2. You should use effective birth control (contraception) during treatment with TALZENNA and for 7 months after the last dose of TALZENNA. Talk to your healthcare provider about forms of birth control that may be right for you.
  3. Tell your healthcare provider right away if you are pregnant or think you are pregnant during treatment with TALZENNA.
Males with female partners who are pregnant or are able to become pregnant:
  1. You should use effective birth control during treatment with TALZENNA and for 4 months after the last dose of TALZENNA.
- are breastfeeding or plan to breastfeed. It is not known if TALZENNA passes into your breast milk. Do not breastfeed during treatment with TALZENNA and for 1 month after the last dose of TALZENNA. Talk to your healthcare provider about the best way to feed your baby during this time.

Tell your healthcare provider about all the medicines you take, including prescription and over-the-counter medicines, vitamins, and herbal supplements. Taking TALZENNA with certain other medicines can affect how TALZENNA works and may cause side effects.
Know the medicines you take. Keep a list of your medicines and show it to your healthcare provider and pharmacist when you get a new medicine.

How should I take TALZENNA?

- Take TALZENNA exactly as your healthcare provider tells you.
- Do not change your dose or stop taking TALZENNA without first talking with your healthcare provider.
- If you are prescribed TALZENNA for breast cancer, take TALZENNA 1 time a day.
- If you are prescribed TALZENNA for prostate cancer:
  - Take TALZENNA with enzalutamide 1 time a day.
  - You should start or continue a gonadotropin-releasing hormone (GnRH) analog therapy during your treatment with TALZENNA and enzalutamide unless you have had a surgery to lower the amount of testosterone in your body (surgical castration).
- Take TALZENNA with or without food.
- Swallow TALZENNA capsules whole. Do not dissolve or open TALZENNA capsules.
- If you vomit or miss a dose of TALZENNA, take your next dose at your regular time. Do not take an extra dose to make up for a missed dose.

What are the possible side effects of TALZENNA?

TALZENNA may cause serious side effects, including:

- See “What is the most important information I should know about TALZENNA?”

The most common side effects of TALZENNA when taken alone include:

- decreased red blood cell counts
- decreased white blood cell counts
- tiredness or weakness
- decreased platelet counts
- increased blood sugar levels
- increased liver function tests
- nausea

- headache
- decreased blood calcium levels
- vomiting
- hair loss
- diarrhea
- decreased appetite

The most common side effects of TALZENNA when taken in combination with enzalutamide include:

- decreased red blood cell counts
- decreased white blood cell counts
- tiredness or weakness
- decreased platelet counts
- decreased calcium in the blood
- nausea
- decreased appetite
- decreased sodium in the blood

- decreased phosphate in the blood
- bone injuries
- decreased magnesium in the blood
- dizziness
- increased bilirubin in the blood
- decreased potassium in the blood
- changes in your sense of taste

TALZENNA may cause fertility problems in males. This may affect your ability to father a child. Talk to your healthcare provider if this is a concern for you.
These are not all of the possible side effects of TALZENNA.
Call your doctor for medical advice about side effects. You may report side effects to FDA at 1-800-FDA-1088.

How should I store TALZENNA?

- Store TALZENNA at 68°F to 77°F (20°C to 25°C).

Keep TALZENNA and all medicines out of the reach of children.

General information about the safe and effective use of TALZENNA.
Medicines are sometimes prescribed for purposes other than those listed in a Patient Information leaflet. Do not use TALZENNA for a condition for which it is not prescribed. Do not give TALZENNA to other people, even if they have the same symptoms that you have. It may harm them. You can ask your healthcare provider or pharmacist for information about TALZENNA that is written for health professionals.

What are the ingredients in TALZENNA?
Active ingredient: talazoparib tosylate
Inactive ingredients: gelatin, glycerol, iron oxide (red), iron oxide (yellow), polyethylene glycol 400, purified water, sorbitol, titanium dioxide, and tocopherol

For more information, go to www.pfizer.com or call 1-800-438-1985.
LAB-1562-2.0

This Patient Information has been approved by the U.S. Food and Drug Administration. Revised: 6/2025

PRINCIPAL DISPLAY PANEL - 0.1 mg Capsule Bottle Label

NDC 0069-0252-30

Pfizer

Talzenna®
(talazoparib) capsules

0.1 mg

30 Capsules
Rx only

PRINCIPAL DISPLAY PANEL - 0.25 mg Capsule Bottle Label

NDC 0069-0353-30

Pfizer

Talzenna®
(talazoparib) capsules

0.25 mg

30 Capsules
Rx only

PRINCIPAL DISPLAY PANEL - 0.35 mg Capsule Bottle Label

NDC 0069-0454-30

Pfizer

Talzenna®
(talazoparib) capsules

0.35 mg

30 Capsules
Rx only

PRINCIPAL DISPLAY PANEL - 0.5 mg Capsule Bottle Label

NDC 0069-0546-30

Pfizer

Talzenna®
(talazoparib) capsules

0.5 mg

30 Capsules
Rx only

PRINCIPAL DISPLAY PANEL - 0.75 mg Capsule Bottle Label

NDC 0069-0655-30

Pfizer

Talzenna®
(talazoparib) capsules

0.75 mg

30 Capsules
Rx only

PRINCIPAL DISPLAY PANEL - 1 mg Capsule Bottle Label

NDC 0069-0757-30

Pfizer

Talzenna®
(talazoparib) capsules

1 mg

30 Capsules
Rx only